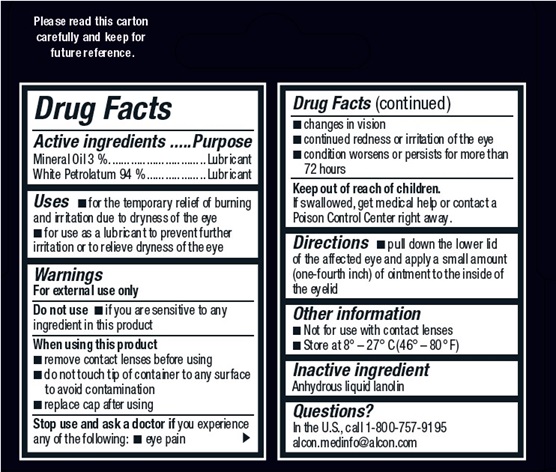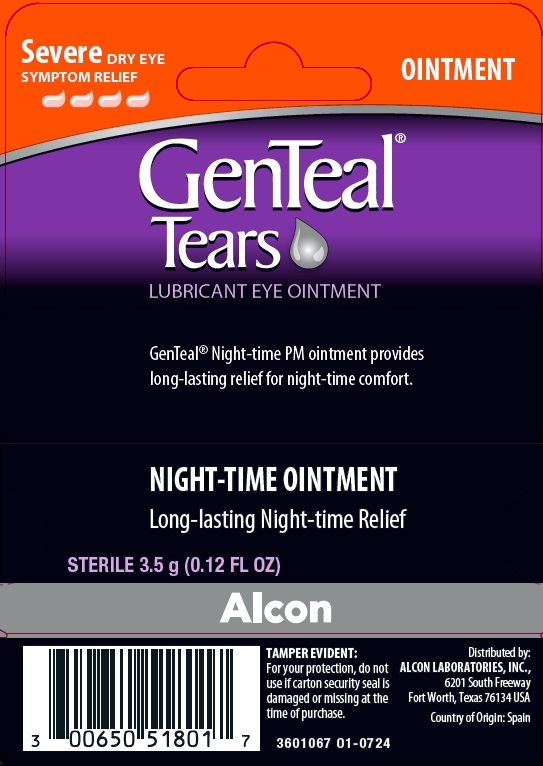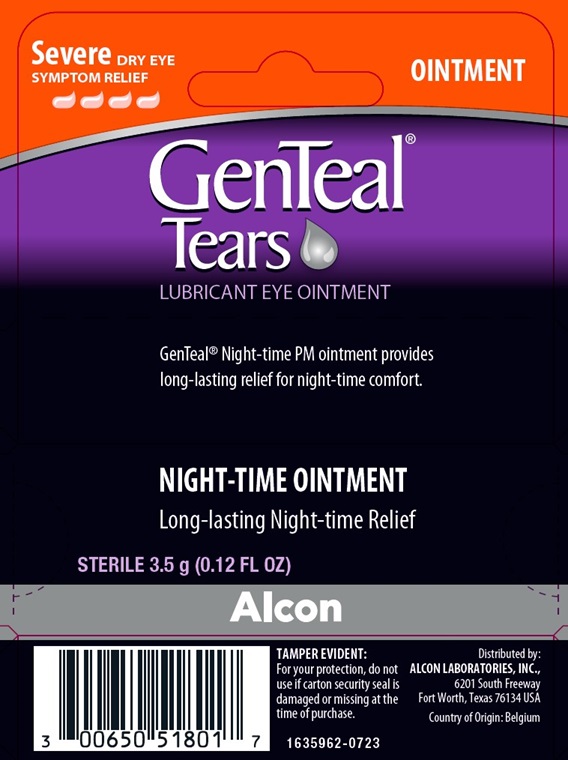 DRUG LABEL: GenTeal 
NDC: 0065-0518 | Form: OINTMENT
Manufacturer: Alcon Laboratories, Inc.
Category: otc | Type: HUMAN OTC DRUG LABEL
Date: 20241205

ACTIVE INGREDIENTS: Mineral Oil 0.03 g/1 g; Petrolatum 0.94 g/1 g
INACTIVE INGREDIENTS: Lanolin

Drug Facts

Active ingredients | Purpose
Mineral oil 3 % | Lubricant
White petrolatum 94 % | Lubricant

Uses

- for use as a lubricant to prevent further irritation
- to relieve dryness of the eye.

Warnings

For external use only

Do not use

- if you are sensitive to any ingredient in this product

When using this product

- do not touch tip of container to any surface
- replace cap after using

Stop use and ask a doctor if you experience any of the following:

- eye pain
- changes in vision
- continued redness or irritation of the eye
- condition worsens or persists for more than 72 hours

Keep out of reach of children

If swallowed, get medical help or contact a Poison Control Center right away.

Directions

Pull down the lower lid of the affected eye and apply a small amount (one-fourth inch) of ointment to the inside of the eyelid.

Other information

store at 8° – 27° C (46° – 80° F).

Inactive ingredient:

Anhydrous liquid lanolin

Questions?

In the U.S., call toll-free 1-800-757-9195
(Mon-Fri 9AM-5PM CST)
alcon.medinfo@alcon.com

PRINCIPAL DISPLAY PANEL

Severe
DRY EYE SYMPTOM RELIEF
OINTMENT
GenTeal®
Tears
LUBRICANT EYE OINTMENT
GenTeal® Night-time PM ointment provides long-lasting relief for night-time comfort.
NIGHT-TIME OINTMENT
Long-lasting Night-time Relief
STERILE 3.5 g (0.12 FL OZ)
Alcon®
TAMPER EVIDENT:
For your protection, do not use if carton security seal is damaged or missing at the time of purchase.
Distributed by:
ALCON LABORATORIES, INC.,
6201 South Freeway
Fort Worth, Texas 76134 USA
Country of Origin: Belgium
1635962-0723
LOT:
EXP.:
Please read this carton carefully and keep for future reference.

Severe
DRY EYE SYMPTOM RELIEF
OINTMENT
GenTeal®
Tears
LUBRICANT EYE OINTMENT
GenTeal® Night-time PM ointment provides long-lasting relief for night-time comfort.
NIGHT-TIME OINTMENT
Long-lasting Night-time Relief
STERILE 3.5 g (0.12 FL OZ)
Alcon
TAMPER EVIDENT:
For your protection, do not use if carton security seal is damaged or missing at the time of purchase.
Distributed by:
ALCON LABORATORIES, INC.,
6201 South Freeway
Fort Worth, Texas 76134 USA
Country of Origin: Spain
3601067 01-0724